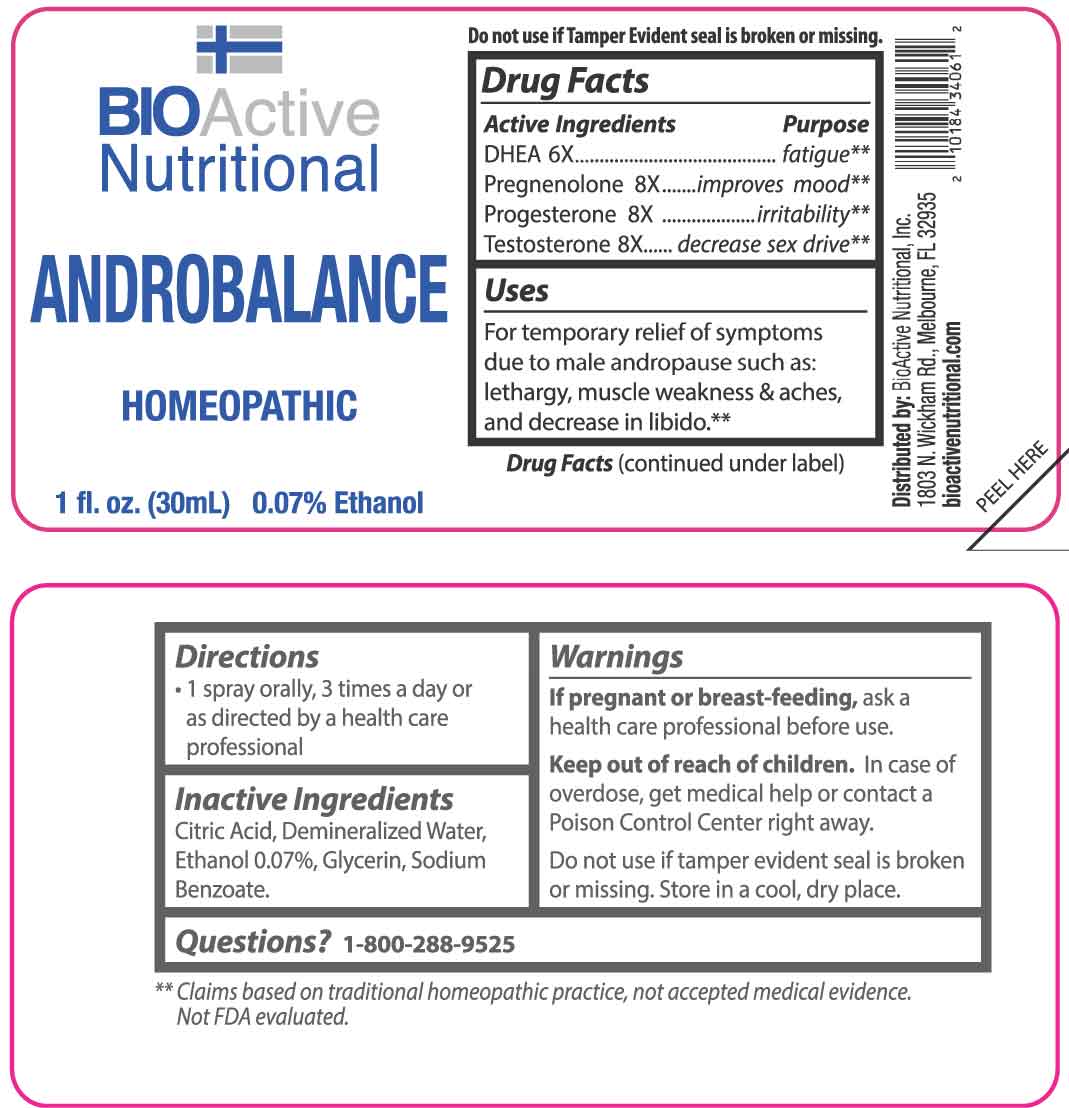 DRUG LABEL: Androbalance
NDC: 43857-0284 | Form: SPRAY
Manufacturer: BioActive Nutritional, Inc.
Category: homeopathic | Type: HUMAN OTC DRUG LABEL
Date: 20251218
DEA Schedule: CIII

ACTIVE INGREDIENTS: PRASTERONE 6 [hp_X]/1 mL; PREGNENOLONE 8 [hp_X]/1 mL; PROGESTERONE 8 [hp_X]/1 mL; TESTOSTERONE 8 [hp_X]/1 mL
INACTIVE INGREDIENTS: GLYCERIN; SODIUM BENZOATE; CITRIC ACID MONOHYDRATE; WATER

DRUG FACTS:

ACTIVE INGREDIENTS:

DHEA 6X, Pregnenolone 8X, Progesterone 8X, Testosterone 8X.

PURPOSE:

DHEA - fatigue,** Pregnenolone - improves mood,** Progesterone - irritability,** Testosterone - decrease sex drive**

**Claims based on traditional homeopathic practice, not accepted medical evidence. Not FDA evaluated.

USES:

For temporary relief of symptoms due to male andropause such as: lethargy, muscle weakness & aches, and decrease in libido.**

**Claims based on traditional homeopathic practice, not accepted medical evidence. Not FDA evaluated.

WARNINGS:

If pregnant or breast-feeding, ask a health care professional before use.

Keep out of reach of children. In case of overdose, get medical help or contact a Poison Control Center right away.

Do not use if tamper evident seal is broken or missing.

Store in a cool, dry place.

KEEP OUT OF REACH OF CHILDREN:

In case of overdose, get medical help or contact a Poison Control Center right away.

DIRECTIONS:

• 1 spray orally, 3 times a day or as directed by a health care professional.

INACTIVE INGREDIENTS:

Citric Acid, Demineralized Water, Ethanol 0.07%, Glycerin, Sodium Benzoate.

QUESTIONS:

Distributed by:

BioActive Nutritional, Inc.
1803 N. Wickham Rd.
Melbourne, FL 32935
bioactivenutritional.com

1-800-288-9525

PACKAGE LABEL DISPLAY:

BIOActive Nutritional

ANDROBALANCE

HOMEOPATHIC

1 fl. oz. (30 mL)